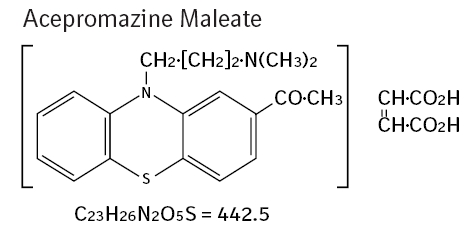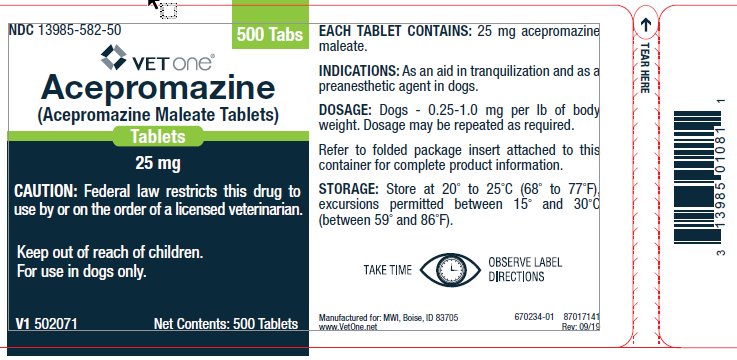 DRUG LABEL: Acepromazine Maleate
NDC: 13985-582 | Form: TABLET
Manufacturer: MWI/VetOne
Category: animal | Type: PRESCRIPTION ANIMAL DRUG LABEL
Date: 20250317

ACTIVE INGREDIENTS: ACEPROMAZINE MALEATE 25 mg/1 1
INACTIVE INGREDIENTS: MICROCRYSTALLINE CELLULOSE; DEXTROSE MONOHYDRATE; STARCH, CORN; MAGNESIUM STEARATE

Acepromazine Maleate Tablets
25 mg

Approved by FDA under NADA # 117-532

For use in dogs only.

Caution:

Federal law restricts this drug to use by or on the order of a licensed veterinarian.

Description:

Acepromazine maleate, a potent neuroleptic agent with a low order of toxicity, is of particular value in the tranquilization of dogs. Its rapid action and lack of hypnotic effect are added advantages.

Chemistry:

2-acetyl-10-(3-dimethyl-aminopropyl) phenothiazine hydrogen maleate.

Mode of Action:

Acepromazine maleate has a depressant effect on the central nervous system and therefore causes sedation, muscular relaxation and a reduction in spontaneous activity. It acts rapidly, exerting a prompt and pronounced calming effect. It is an effective preanesthetic agent and lowers the dosage requirement of general anesthetics.

Indications:

As an aid in tranquilization and as a preanesthetic agent in dogs.

Acepromazine Tablets can be used as an aid in controlling intractable animals during examination, treatment, grooming, x-ray and minor surgical procedures.

Dosage and Administration:

Dogs: 0.25 - 1.0 mg/lb of body weight. Dosage may be repeated as required.

Animal Safety:

Acute and chronic toxicity studies have shown a very low order of toxicity for acepromazine maleate.

A safety study using elevated dosages of acepromazine maleate demonstrated no adverse reactions even when administered at three times the upper limit of the recommended daily dosage (3.0 mg/lb body weight). The clinical observation for this high dosage was mild depression which disappeared in most dogs 24 hours after termination of dosing.

The only occurrence of adverse reaction during numerous clinical trials was a very mild respiratory distress (reverse sneeze) which was transient in nature and had no effect on the desired action of the drug.

Contraindications:

Phenothiazines may potentiate the toxicity of organophosphates. Therefore, do not use acepromazine maleate to control tremors associated with organic phosphate poisoning.

Do not use in conjunction with organophosphorus vermifuges or ectoparasiticides, including flea collars.

Do not use with procaine hydrochloride.

Warning:

Do not use in animals intended for human consumption.

Precautions:

Tranquilizers are potent central nervous system depressants, and they can cause marked sedation with suppression of the sympathetic nervous system. Tranquilizers can produce prolonged depression or motor restlessness when given in excessive amounts or when given to sensitive animals. Tranquilizers are additive in action to the actions of other depressants and will potentiate general anesthesia. Tranquilizers should be administered in smaller doses and with greater care during general anesthesia and also to animals exhibiting symptoms of stress, debilitation, cardiac disease, sympathetic blockade, hypovolemia or shock. Acepromazine, like other phenothiazine derivatives, is detoxified in the liver; therefore, it should be used with caution on animals with a previous history of liver dysfunction or leukopenia.

Epinephrine is contraindicated for treatment of acute hypotension produced by phenothiazine-derivative tranquilizers since further depression of blood pressure can occur.

Phenothiazines should be used with caution when followed by epidural anesthetic procedures because they may potentiate the arterial hypotensive effects of local anesthetics.

Adverse Reactions:

A few rare but serious occurrences of idiosyncratic reactions to acepromazine may occur in dogs following oral or parenteral administration. These potentially serious adverse reactions include behavioral disorders in dogs such as aggression, biting/chewing, and nervousness.

To report suspected adverse reactions, to obtain a Safety Data Sheet or for technical assistance, call 1-888-637-4251. For additional information about adverse drug experience reporting for animal drugs, contact FDA at 1-888-FDA-VETS, or www.fda.gov/reportanimalae.

Storage:

Store at 20° to 25°C (68° to 77°F), excursions permitted between 15° and 30°C (between 59° and 86°F).

How Supplied:

Acepromazine Maleate Tablets are available in 10 and 25 mg quarter-scored tablets and are supplied in bottles containing 100 and 500 tablets.

NDC 13985-583-10 – 10 mg – 100 tablets

NDC 13985-583-50 – 10 mg – 500 tablets

NDC 13985-582-25 – 25 mg – 100 tablets

NDC 13985-582-50 – 25 mg – 500 tablets

Manufactured for: MWI

Boise, ID 83705

www.VetOne.net

Rev: 09/19

Principal Display Panel - Container Label, 25 mg, 500 Tablets

NDC 13985-582-50 500 Tabs

VETONE®

Acepromazine

(Acepromazine Maleate Tablets)

25 mg

CAUTION: Federal law restricts this drug to use by or on the order of a licensed veterinarian.

Keep out of reach of children.

For use in dogs only

V1 502071 Net Contents: 500 Tablets